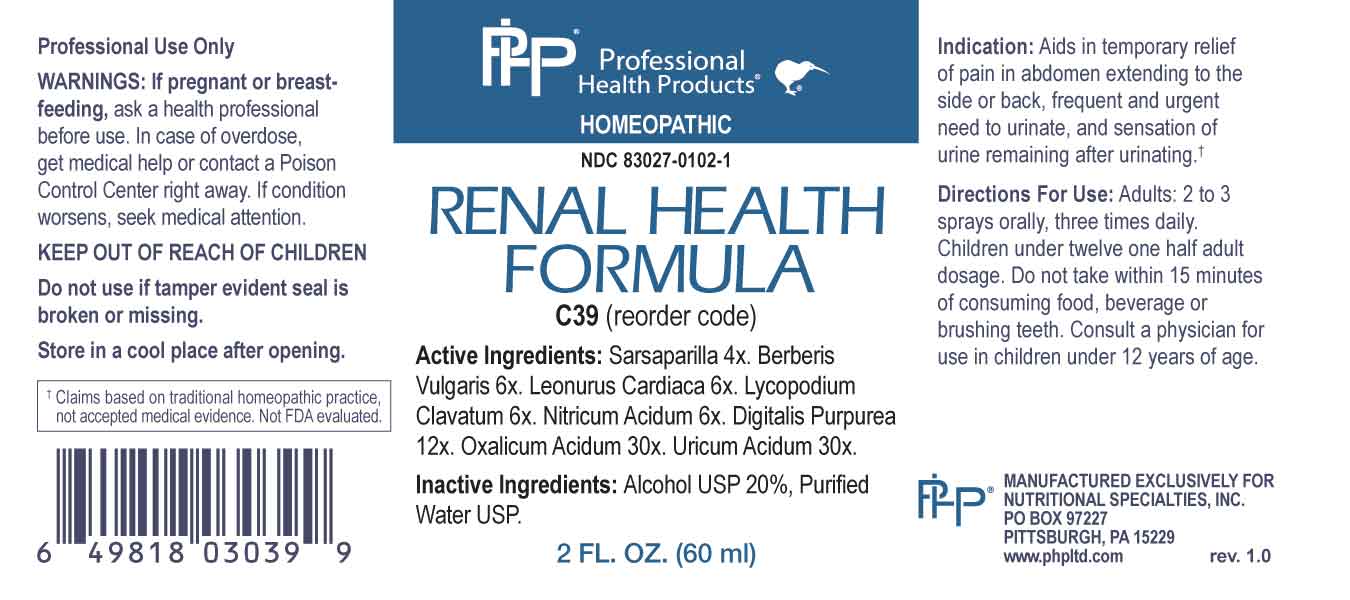 DRUG LABEL: Renal Health Formula
NDC: 83027-0102 | Form: SPRAY
Manufacturer: Nutritional Specialties, Inc.
Category: homeopathic | Type: HUMAN OTC DRUG LABEL
Date: 20230823

ACTIVE INGREDIENTS: SMILAX ORNATA ROOT 4 [hp_X]/1 mL; BERBERIS VULGARIS ROOT BARK 6 [hp_X]/1 mL; LEONURUS CARDIACA WHOLE 6 [hp_X]/1 mL; LYCOPODIUM CLAVATUM SPORE 6 [hp_X]/1 mL; NITRIC ACID 6 [hp_X]/1 mL; DIGITALIS 12 [hp_X]/1 mL; OXALIC ACID DIHYDRATE 30 [hp_X]/1 mL; URIC ACID 30 [hp_X]/1 mL
INACTIVE INGREDIENTS: WATER; ALCOHOL

DRUG FACTS:

ACTIVE INGREDIENTS:

Sarsaparilla 4X, Berberis Vulgaris 6X, Leonurus Cardiaca 6X, Lycopodium Clavatum 6X, Nitricum Acidum 6X, Digitalis Purpurea 12X, Oxalicum Acidum 30X, Uricum Acidum 30X.

PURPOSE:

Aids in temporary relief of Pain in abdomen extending to the side or back, frequent and urgent need to urinate, and sensation of urine remaining after urinating.†

†Claims based on traditional homeopathic practice, not accepted medical evidence. Not FDA evaluated.

WARNINGS:

Professional Use Only

If pregnant or breast-feeding, ask a health professional before use.

In case of overdose, get medical help or contact a Poison Control Center right away.

If condition worsens, seek medical attention.

KEEP OUT OF REACH OF CHILDREN

Do not use if tamper evident seal is broken or missing.

Store in a cool place after opening

KEEP OUT OF REACH OF CHILDREN:

In case of overdose, get medical help or contact a Poison Control Center right away.

DIRECTIONS:

Adults: 2 to 3 sprays orally, three times daily. Children under twelve one half adult dosage. Do not take within 15 minutes of consuming food, beverage or brushing teeth. Consult a physician for use in children under 12 years of age.

INDICATIONS:

Aids in temporary relief of Pain in abdomen extending to the side or back, frequent and urgent need to urinate, and sensation of urine remaining after urinating.†

†Claims based on traditional homeopathic practice, not accepted medical evidence. Not FDA evaluated.

INACTIVE INGREDIENTS:

Alcohol USP 20%, Purified Water USP.

QUESTIONS:

MANUFACTURED EXCLUSIVELY FOR

NUTRITIONAL SPECIALTIES, INC.

PO BOX 97227

PITTSBURG, PA 15229

www.phpltd.com

PACKAGE LABEL DISPLAY:

Professional

Health Products

HOMEOPATHIC

NDC 83027-0102-1

RENAL HEALTH

FORMULA

2 FL. OZ (60 ml)